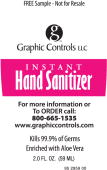 DRUG LABEL: Instant Hand Sanitizer
NDC: 49959-1111 | Form: GEL
Manufacturer: Graphic Controls
Category: otc | Type: HUMAN OTC DRUG LABEL
Date: 20091109

ACTIVE INGREDIENTS: Alcohol .60 g/1 mL
INACTIVE INGREDIENTS: Aloe; D&C Green No. 5; D&C Yellow No. 10; Water

Instant Hand Sanitizer

Active ingredient

Ethyl Alcohol 66.5%

Pupose

Antiseptic

Uses

- for handwashing to decrease bacteria on skin
- recommended for repeated use

Warnings

For external use only. Flammable, keep away from fire or flame.

Do not use in the eyes. If this happens, rinse thoroughly with water

Stop use and ask a doctor if irritation and redness develop and persists for more than 72 hours

Keep out of reach of children

If ingested get medical help or contact a Poison Control Center right away

Directions

- wet hands thorough with product
- allow to dry without wiping
- children under 6 should be supervised while using this product

Inactive ingredients

aloe vera, carbomer, D&C green #5, D&C yellow #10, fragrance, purified water, triethanolamine

Manufactured for Graphic Controls LLC
Buffalo, NY 14204
1-800-669-1535

PACKAGE LABEL - PRINCIPAL DISPLAY PANEL – BOTTLE

FREE Sample-Not for Resale

GRAPHIC CONTROLS LLC – Instant Hand Sanitizer

For more information or To Order call

800-665-1535

www.graphiccontrols.com

Kills 99.99% of Germs

Enriched with Aloe Vera